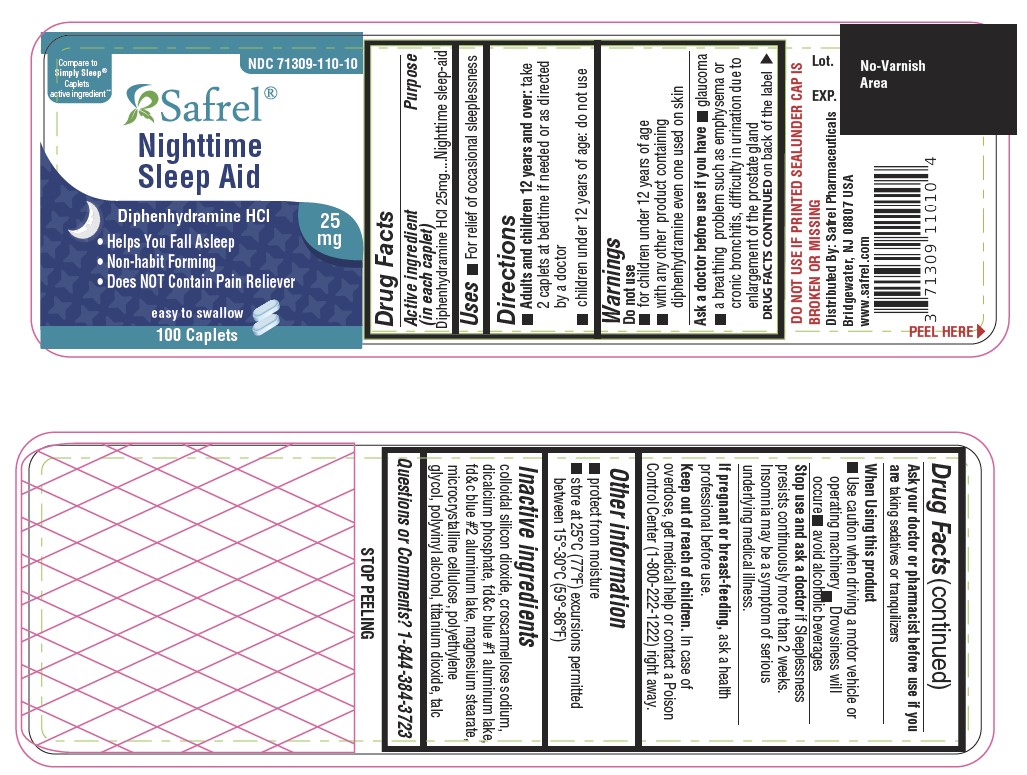 DRUG LABEL: Sleep-EZ Nighttime Sleep Aid
NDC: 71309-110 | Form: TABLET, COATED
Manufacturer: Safrel Pharmaceuticals, LLC.
Category: otc | Type: HUMAN OTC DRUG LABEL
Date: 20210531

ACTIVE INGREDIENTS: DIPHENHYDRAMINE HYDROCHLORIDE 25 mg/1 1
INACTIVE INGREDIENTS: CELLULOSE, MICROCRYSTALLINE; TITANIUM DIOXIDE; POLYVINYL ALCOHOL; POLYETHYLENE GLYCOL, UNSPECIFIED; TALC; FD&C BLUE NO. 1; FD&C BLUE NO. 2; SILICON DIOXIDE; CROSCARMELLOSE SODIUM; ANHYDROUS DIBASIC CALCIUM PHOSPHATE; MAGNESIUM STEARATE

Sleep-EZ Nighttime Sleep Aid

Active ingredient (in each caplet)

Diphenhydramine HCl 25 mg

Purpose

Nighttime sleep-aid

Uses

provides relief of occasional sleeplessness

Warnings

Do not use

- for children under 12 years of age
- with any other product containing diphenhydramine, even one used on skin
- with other drugs that cause drowsiness such as antihistamines and nighttime cold/flu products

Ask a doctor before use if you have

- a breathing problem such as emphysema or chronic bronchitis
- trouble urinating due to an enlarged prostate gland
- glaucoma
- heart disease

Ask a doctor or pharmacist before use if you are

taking sedative or tranquilizers or any other sleep-aid

When using this product

- drowsiness will occur
- avoid alcoholic beverages and other drugs that cause drowsiness
- excitability may occur, especially in children
- alcohol, sedatives and tranquilizers may increase drowsiness
- be careful when driving a motor vehicle or operating machinery

Stop use and ask a doctor if

sleeplessness persists continuously for more than 2 weeks. Insomnia may be a symptom of a serious underlying medical illness.

If pregnant or breast-feeding

ask a health professional before use.

Keep out of reach of children.

Overdose warning: Taking more than directed can cause serious health problems. In case of overdose, get medical help or contact a Poison Control Center (1-800-222-1222) right away. Quick medical attention is critical for adults as well as for children even if you do not notice any signs or symptoms.

Directions

- do not take more than directed (see overdose warning)
- adults and children 12 years of age and over: - take 2 caplets at bedtime if needed or as directed by a doctor
- children under 12 years of age: do not use

Other Information

- Each caplet contains: Calcium 23.52 mg
- store at 25°C (77°F); excursions permitted between 15°-30°C (59°-86°F)
- read all product information before using
- TAMPER EVIDENT: DO NOT USE IF IMPRINTED SAFETY SEAL UNDER CAP IS BROKEN OR MISSING

Inactive Ingredients

Colloidal silicon dioxide, Croscarmellose sodium, Dicalcium phosphate, FD&C Blue #1, FD&C Blue #2, Magnesium stearate, Microcrystalline cellulose, Polyethylene glycol, Polyvinyl alcohol, Talc, Titanium dioxide

Questions or comments?

Call toll free 1-844-384-3723 Monday through Friday 9AM – 5PM EST or www.safrel.com

Principal Display Panel

Compare to Tylenol® Simply Sleep active ingredients*

* This product is not manufactured or distributed by McNeil Consumer Healthcare, owner of the registered trademark Simply Sleep®.

Diphenhydramine HCl Tablets, 25 mg